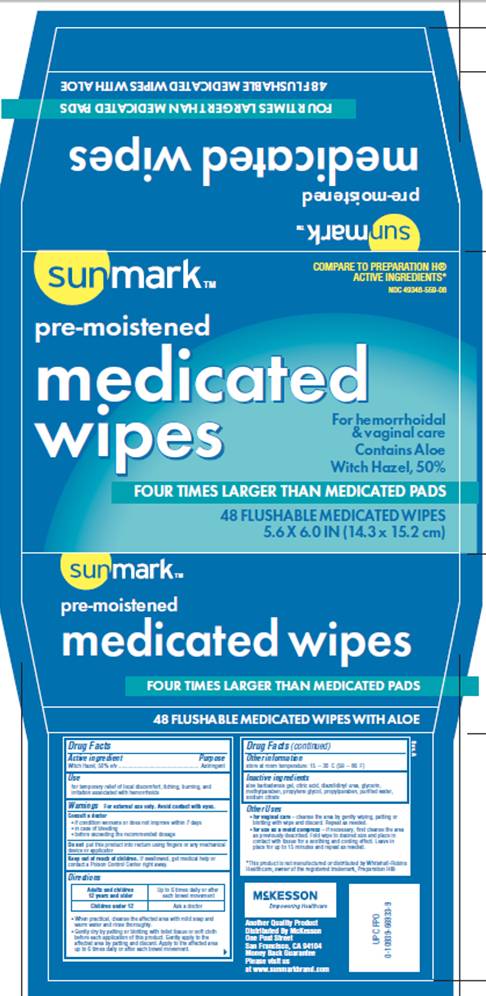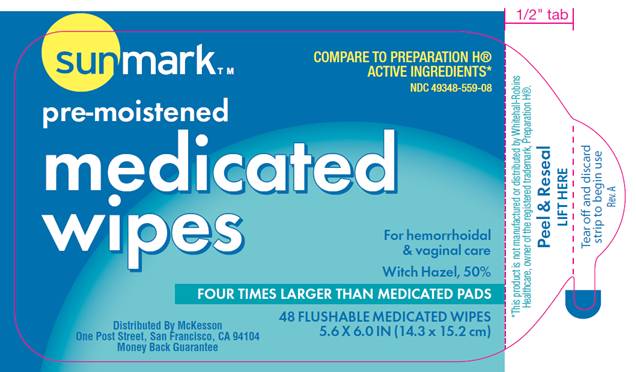 DRUG LABEL: Medicated Wipes
NDC: 49348-559 | Form: SOLUTION
Manufacturer: McKesson
Category: otc | Type: HUMAN OTC DRUG LABEL
Date: 20100212

ACTIVE INGREDIENTS: witch hazel 0.50 mL/1 mL
INACTIVE INGREDIENTS: aloe vera leaf; citric acid monohydrate; diazolidinylurea; glycerin; methylparaben; propylene glycol; propylparaben; sodium citrate; water

DRUG FACTS

ACTIVE INGREDIENT

Witch Hazel 50% v/v

PURPOSE

Astringent

USE

For temporary relief of local discomfort, burning, and irritation associated with hemorrhoids

WARNINGS

For external use only. Avoid contact with eyes.

Consult a doctor

- if condition worsens or does not improve within 7 days
- in case of bleeding
- before exceeding the recommended dosage

Do not

put this product into rectum using fingers or any mechanical device or applicator

Keep out of reach of children

If swallowed, get medical help or contact a Poison Control Center right away.

DIRECTIONS

- When practical, cleanse the affected area with mild soap and warm water and rinse thoroughly.
- Gently dry by patting or blotting with toilet tissue or soft cloth before each application of this product. Gently apply to the affected area by patting and then discard. Apply to the affected area up to 6 times daily or after each bowel movement.
- Children under 12 years of age: consult a doctor.

OTHER INFORMATION

Store at room temperature: 15°- 30° C (59° - 86° F)

Other uses

- for vaginal care - cleanse the area by gently wiping, patting or blotting with pad and discard. Repeat as needed.
- for use as a moist compress - if necessary, first cleanse the area as previously described. Fold wipe to desired size and place in contact with tissue for a soothing and cooling effect. Leave in place for up to 15 minutes and repeat as needed.

INACTIVE INGREDIENTS

aloe barbadensis gel, citric acid, diazolidinyl urea, glycerin, methylparaben, propylene glycol, propylparaben, purified water, sodium citrate

PACKAGE INFORMATION - PEEL AWAY LABEL

Sunmark TM

COMPARE TO PREPARATION H® ACTIVE INGREDIENTS*
NDC 49348-559-08

pre-moistened
medicated wipes
for hemorrhoidal and vaginal care
Witch Hazel, 50%
FOUR TIMES LARGER THAN MEDICATED PADS
48 FLUSHABLE MEDICATED WIPES
5.6 X 6.0 IN (14.3 X 15.2 cm)
Distributed by McKesson
One Post Street, San Francisco, CA 94104
Money Back Guarantee
*This product is not manufactured or distributed by Whitehail-Robins Healthcare, owner of the registered trademark PREPARATION H®.
Peel and Reseal
LIFT HERE
Tear off and discard strip to begin use
Rev. A

PACKAGE INFORMATION - SLEEVE

Sunmark TM
COMPARE TO PREPARATION H® ACTIVE INGREDIENTS*
NDC 49348-559-08
pre-moistened
medicated wipes
For hemorrhoidal and vaginal care
Contains Aloe
Witch Hazel, 50%
FOUR TIMES LARGER THAN MEDICATED PADS
48 FLUSHABLE MEDICATED WIPES
5.6 X 6.0 IN (14.3 X 15.2 cm)
*This product is not manufactured or distributed by Whitehail-Robins Healthcare, owner of the registered trademark PREPARATION H®.
Another Quality Product
Distributed by McKesson
One Post Street, San Francisco, CA 94104
Money Back Guarantee
Please visit us
at www.sunmarkbrand.com